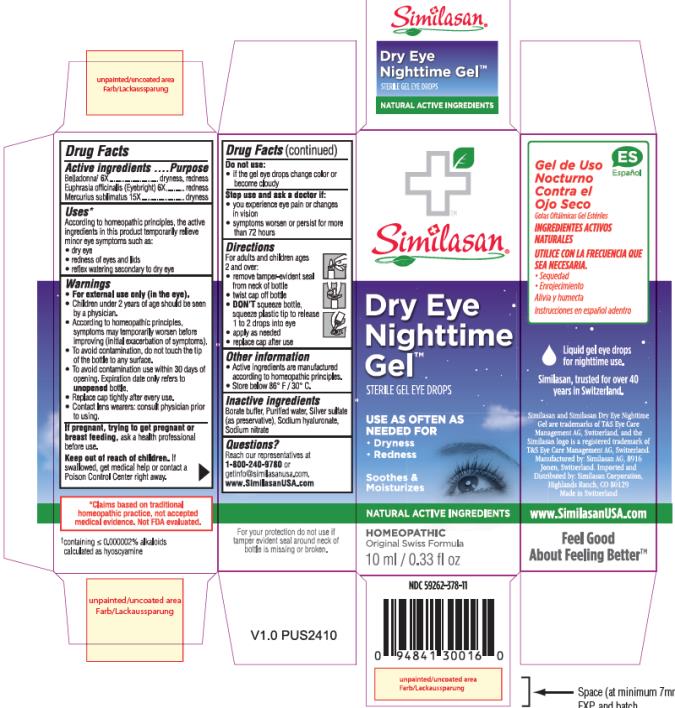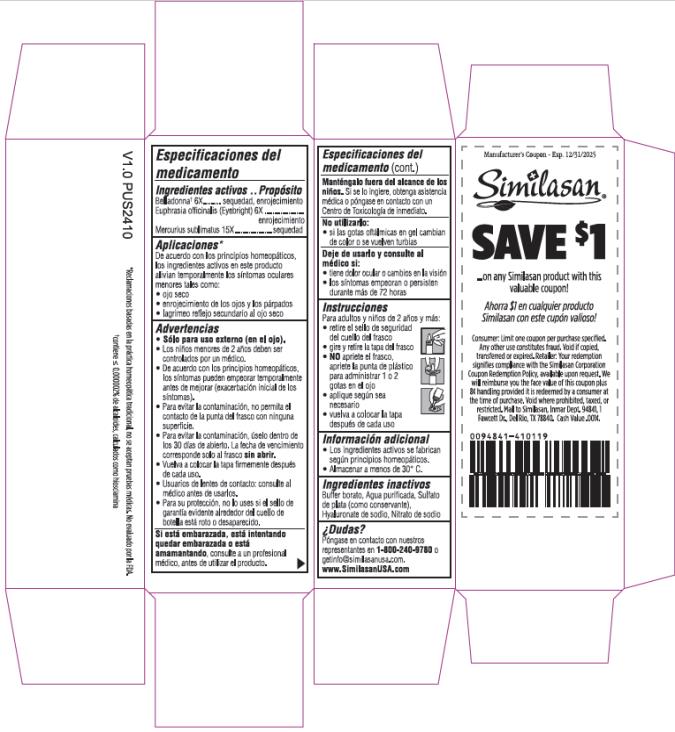 DRUG LABEL: Dry Eye Nighttime
NDC: 59262-378 | Form: GEL
Manufacturer: Similasan Corporation
Category: homeopathic | Type: HUMAN OTC DRUG LABEL
Date: 20220120

ACTIVE INGREDIENTS: ATROPA BELLADONNA 6 [hp_X]/10 mL; EUPHRASIA STRICTA 6 [hp_X]/10 mL; MERCURIC CHLORIDE 15 [hp_X]/10 mL
INACTIVE INGREDIENTS: WATER; SILVER SULFATE; HYALURONATE SODIUM; SODIUM NITRATE

Dry Eye Nighttime Gel

Active Ingredient

Belladonna* 6X

Purpose

dryness, redness

Active Ingredient

Euphrasia officinalis (Eyebright) 6X

Purpose

redness

Active Ingredient

Mercurius sublimatus 15X

Purpose

dryness

Uses:

According to homeopathic principles, the active ingredients in this medication temporarily relieve minor symptoms such as:

- dry eye
- redness of eyes and lids
- reflex watering secondary to dry eye

Warnings:

- For external use only (in the eye).
- Children under 2 years of age should be seen by a physician.
- According to homeopathic principles, symptoms may temporarily worsen before improving (initial exacerbation of symptoms).
- To avoid contamination, do not touch the tip of the container to any surface.
- To avoid contamination use within 30 days of opening. Expiration date only refers to unopened bottle.
- Replace cap tightly after every use.
- Contact lens wearers: consult physician prior to using.

If pregnant, trying to get pregnant or breast feeding,

ask a health professional before use.

Keep out of reach of children.

If swallowed, get medical help or contact a Poison Control Center right away.

Do not use:

if the gel changes color or becomes cloudy

Stop use and ask a doctor if:

- you experience eye pain or changes in vision
- symptoms worsen or persist for more than 72 hours

Directions:

For adults and children age 2 and over:

- remove tamper-evident seal from neck of bottle
- twist cap off bottle
- DON’T squeeze bottle, squeeze plastic tip to release 1 to 2 drops into eye
- apply as needed
- replace cap after use

Other Information:

- Active ingredients are manufactured according to homeopathic principles.
- Store below 86° F / 30° C

Inactive Ingredients

Borate buffer, Purified water, Silver sulphate (as preservative), Sodium hyaluronate, Sodium nitrate

Questions?

Reach our representatives at 1-800-240-9780 or getinfo@similasanusa.com.
www.SimilasanUSA.com

*containing ≤0.000002% alkaloids calculated as hyoscyamine

Principle Display Panel

Similasan
Dry Eye Nighttime Gel
Sterile Gel Eye Drops
10 ml / 0.33 fl oz